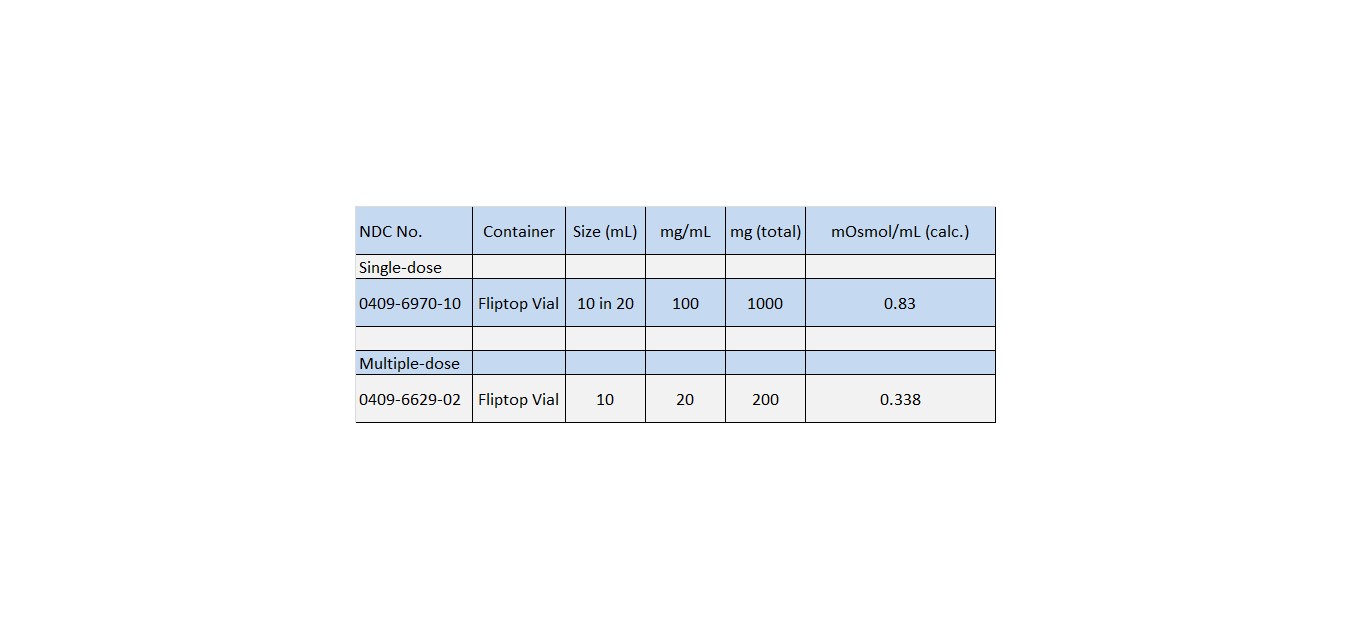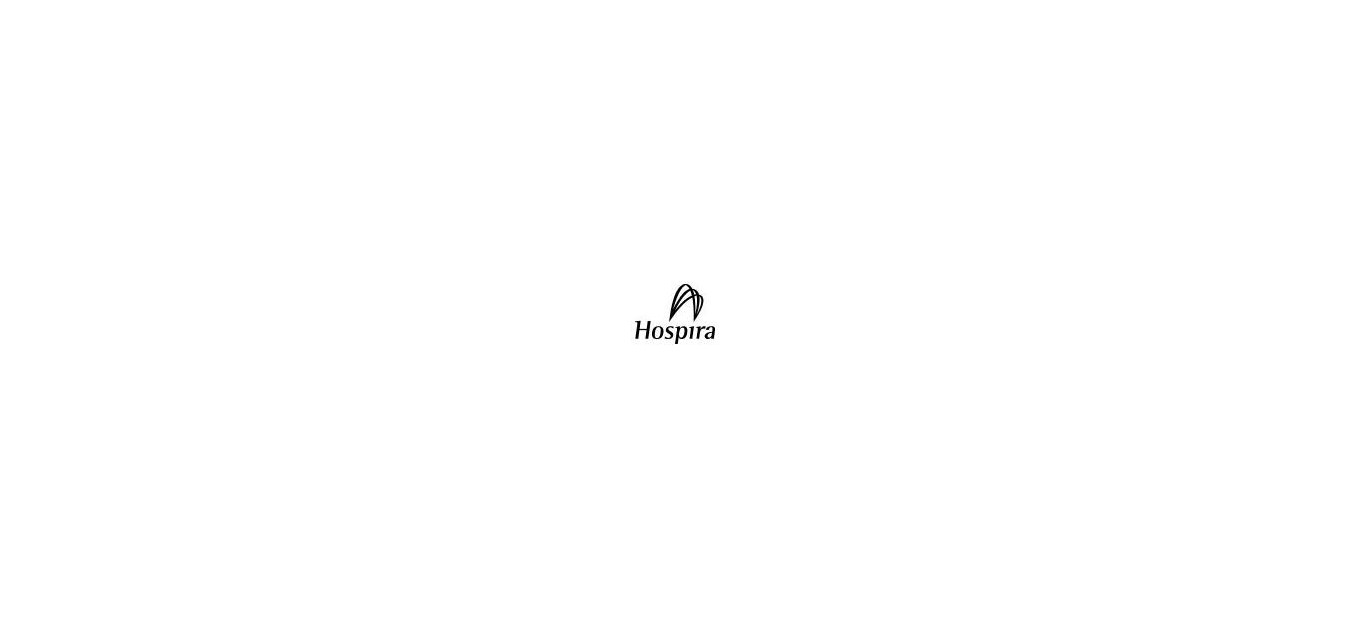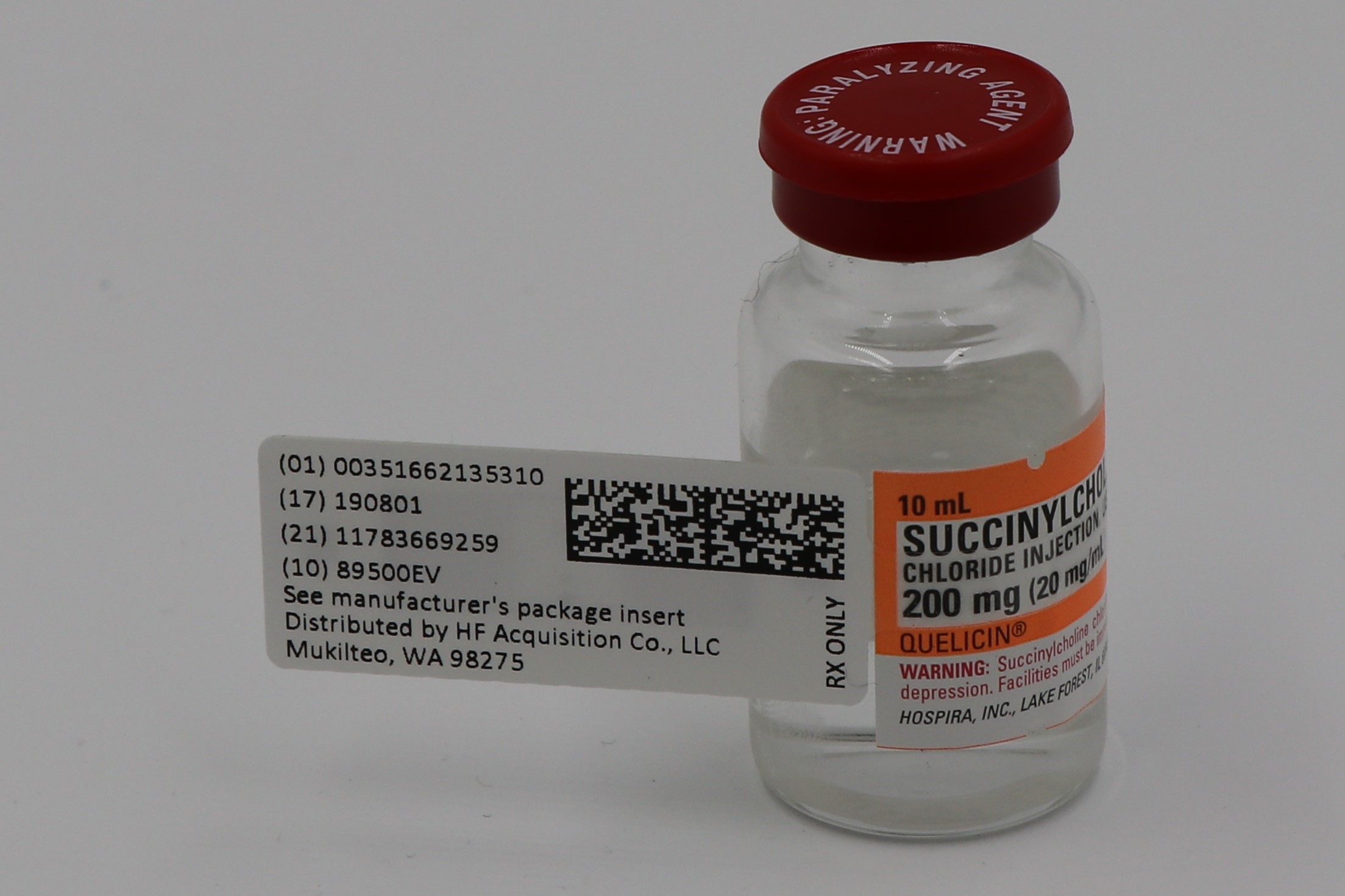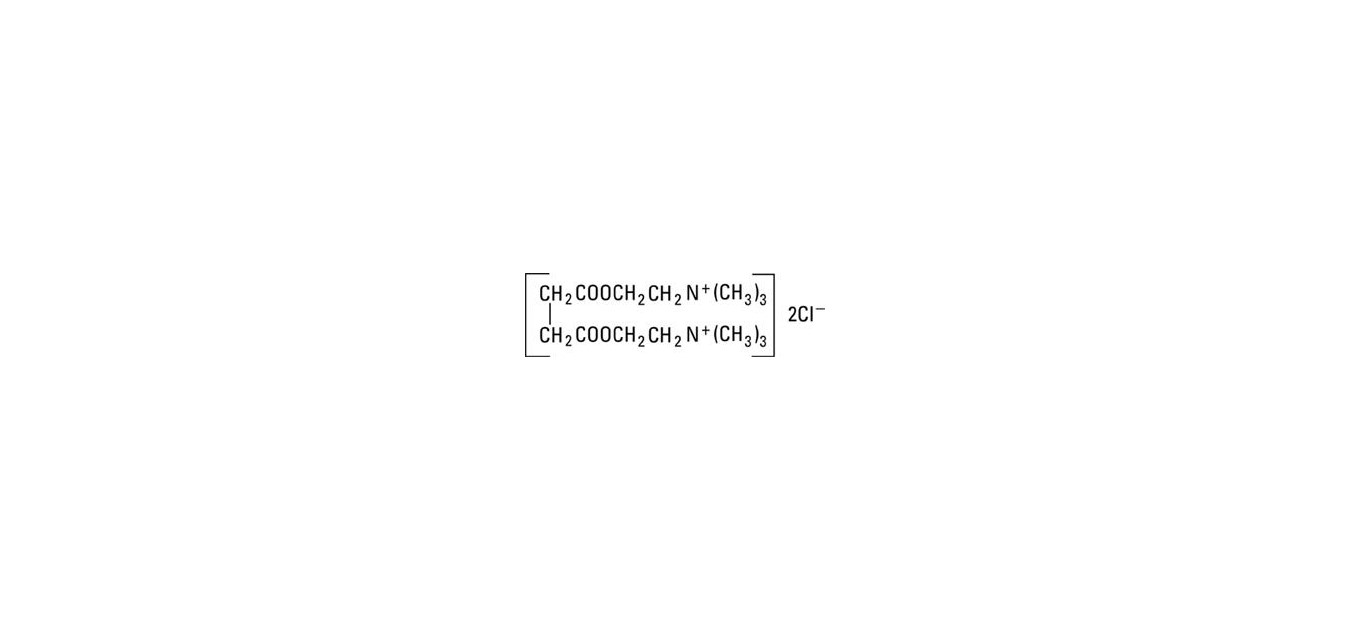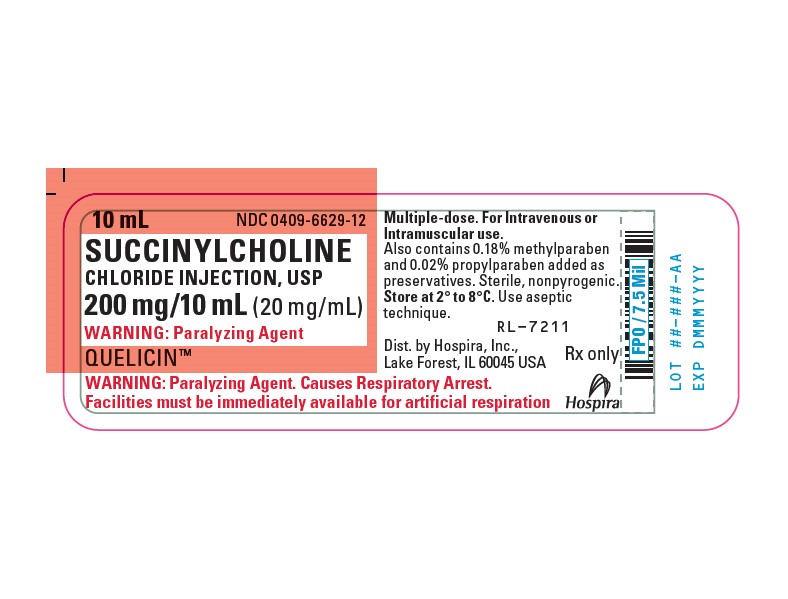 DRUG LABEL: SUCCINYLCHOLINE CHLORIDE
NDC: 51662-1353 | Form: INJECTION, SOLUTION
Manufacturer: HF Acquisition Co LLC, DBA HealthFirst
Category: prescription | Type: HUMAN PRESCRIPTION DRUG LABEL
Date: 20200225

ACTIVE INGREDIENTS: SUCCINYLCHOLINE CHLORIDE 20 mg/1 mL
INACTIVE INGREDIENTS: HYDROCHLORIC ACID; PROPYLPARABEN 0.2 mg/1 mL; SODIUM HYDROXIDE; SODIUM CHLORIDE; METHYLPARABEN 1.8 mg/1 mL

SUCCINYLCHOLINE CHLORIDE INJECTION, USP 200mg (20mg/mL) 10mL VIAL

BOXED WARNING

WARNING

RISK OF CARDIAC ARREST FROM HYPERKALEMIC RHABDOMYOLYSIS

There have been rare reports of acute rhabdomyolysis with hyperkalemia followed by ventricular dysrhythmias, cardiac arrest and death after the administration of succinylcholine to apparently healthy pediatric patients who were subsequently found to have undiagnosed skeletal muscle myopathy, most frequently Duchenne's muscular dystrophy.

This syndrome often presents as peaked T-waves and sudden cardiac arrest within minutes after the administration of the drug in healthy appearing pediatric patients (usually, but not exclusively, males, and most frequently 8 years of age or younger). There have also been reports in adolescents.

Therefore, when a healthy appearing infant or child develops cardiac arrest soon after administration of succinylcholine, not felt to be due to inadequate ventilation, oxygenation or anesthetic overdose, immediate treatment for hyperkalemia should be instituted. This should include administration of intravenous calcium, bicarbonate, and glucose with insulin, with hyperventilation. Due to the abrupt onset of this syndrome, routine resuscitative measures are likely to be unsuccessful. However, extraordinary and prolonged resuscitative efforts have resulted in successful resuscitation in some reported cases. In addition, in the presence of signs of malignant hyperthermia, appropriate treatment should be instituted concurrently.

Since there may be no signs or symptoms to alert the practitioner to which patients are at risk, it is recommended that the use of succinylcholine in pediatric patients should be reserved for emergency intubation or instances where immediate securing of the airway is necessary, e.g., laryngospasm, difficult airway, full stomach, or for intramuscular use when a suitable vein is inaccessible (see PRECAUTIONS: Pediatric Use and DOSAGE & ADMINISTRATION).

SPL UNCLASSIFIED

A short-acting depolarizing skeletal muscle relaxant.

SPL UNCLASSIFIED

This drug should be used only by individuals familiar with its actions, characteristics and hazards.

DESCRIPTION

QUELICIN (Succinylcholine Chloride Injection, USP) is a sterile, nonpyrogenic solution to be used as an ultra short-acting, depolarizing, skeletal muscle relaxant See HOW SUPPLIED for summary of content and characteristics of the solutions. The solutions are for intramuscular (IM) or intravenous (IV) use.

Succinylcholine Chloride, USP is chemically designated C14H30Cl2N2O4 and its molecular weight is 361.31.

It has the following structural formula:

Succinylcholine is a diquaternary base consisting of the dichloride salt of the dicholine ester of succinic acid. It is a white, odorless, slightly bitter powder, very soluble in water. The drug is incompatible with alkaline solutions but relatively stable in acid solutions. Solutions of the drug lose potency unless refrigerated.

Solution intended for multiple-dose administration contains 0.18% methylparaben and 0.02% propylparaben as preservatives (List No. 6629). Solution intended for single-dose administration contains no preservatives. Unused solution should be discarded. Product not requiring dilution (multiple-dose fliptop vial) contains sodium chloride to render isotonic. May contain sodium hydroxide and/or hydrochloric acid for pH adjustment. pH is 3.6 (3.0 to 4.5). See table in HOW SUPPLIED for characteristics.

Sodium Chloride, USP, chemically designated NaCl, is a white crystalline compound freely soluble in water.

CLINICAL PHARMACOLOGY

Succinylcholine is a depolarizing skeletal muscle relaxant. As does acetylcholine, it combines with the cholinergic receptors of the motor end plate to produce depolarization. This depolarization may be observed as fasciculations. Subsequent neuromuscular transmission is inhibited so long as adequate concentration of succinylcholine remains at the receptor site. Onset of flaccid paralysis is rapid (less than one minute after intravenous administration), and with single administration lasts approximately 4 to 6 minutes.

Succinylcholine is rapidly hydrolyzed by plasma cholinesterase to succinylmonocholine (which possesses clinically insignificant depolarizing muscle relaxant properties) and then more slowly to succinic acid and choline (see PRECAUTIONS). About 10% of the drug is excreted unchanged in the urine. Succinylcholine levels were reported to be below the detection limit of 2 µg/mL after 2.5 minutes of an IV bolus dose of 1 or 2 mg/kg in fourteen (14) anesthetized patients. The paralysis following administration of succinylcholine is progressive, with differing sensitivities of different muscles. This initially involves consecutively the levator muscles of the face, muscles of the glottis and finally the intercostals and the diaphragm and all other skeletal muscles.

Succinylcholine has no direct action on the uterus or other smooth muscle structures. Because it is highly ionized and has low fat solubility, it does not readily cross the placenta.

Tachyphylaxis occurs with repeated administration (see PRECAUTIONS).

Depending on the dose and duration of succinylcholine administration, the characteristic depolarizing neuromuscular block (Phase I block) may change to a block with characteristics superficially resembling a non-depolarizing block (Phase II block). This may be associated with prolonged respiratory muscle paralysis or weakness in patients who manifest the transition to Phase II block. When this diagnosis is confirmed by peripheral nerve stimulation, it may sometimes be reversed with anticholinesterase drugs such as neostigmine (see PRECAUTIONS). Anticholinesterase drugs may not always be effective. If given before succinylcholine is metabolized by cholinesterase, anticholinesterase drugs may prolong rather than shorten paralysis.

Succinylcholine has no direct effect on the myocardium. Succinylcholine stimulates both autonomic ganglia and muscarinic receptors which may cause changes in cardiac rhythm, including cardiac arrest. Changes in rhythm, including cardiac arrest, may also result from vagal stimulation, which may occur during surgical procedures, or from hyperkalemia, particularly in pediatric patients (see PRECAUTIONS: Pediatric Use). These effects are enhanced by halogenated anesthetics.

Succinylcholine causes an increase in intraocular pressure immediately after its injection and during the fasciculation phase, and slight increases which may persist after onset of complete paralysis (see WARNINGS).

Succinylcholine may cause slight increases in intracranial pressure immediately after its injection and during the fasciculation phase (see PRECAUTIONS).

As with other neuromuscular blocking agents, the potential for releasing histamine is present following succinylcholine administration. Signs and symptoms of histamine mediated release such as flushing, hypotension and bronchoconstriction are, however, uncommon in normal clinical usage.

Succinylcholine has no effect on consciousness, pain threshold or cerebration. It should be used only with adequate anesthesia (see WARNINGS).

INDICATIONS & USAGE

Succinylcholine chloride is indicated as an adjunct to general anesthesia, to facilitate tracheal intubation, and to provide skeletal muscle relaxation during surgery or mechanical ventilation.

CONTRAINDICATIONS

Succinylcholine is contraindicated in persons with personal or familial history of malignant hyperthermia, skeletal muscle myopathies and known hypersensitivity to the drug. It is also contraindicated in patients after the acute phase of injury following major burns, multiple trauma, extensive denervation of skeletal muscle, or upper motor neuron injury, because succinylcholine administered to such individuals may result in severe hyperkalemia which may result in cardiac arrest (see WARNINGS). The risk of hyperkalemia in these patients increases over time and usually peaks at 7 to 10 days after the injury. The risk is dependent on the extent and location of the injury. The precise time of onset and the duration of the risk period are not known.

WARNINGS

Succinylcholine should be used only by those skilled in the management of artificial respiration and only when facilities are instantly available for tracheal intubation and for providing adequate ventilation of the patient, including the administration of oxygen under positive pressure and the elimination of carbon dioxide. The clinician must be prepared to assist or control respiration.

To avoid distress to the patient, succinylcholine should not be administered before unconsciousness has been induced. In emergency situations, however, it may be necessary to administer succinylcholine before unconsciousness is induced.

Succinylcholine is metabolized by plasma cholinesterase and should be used with caution, if at all, in patients known to be or suspected of being homozygous for the atypical plasma cholinesterase gene.

Anaphylaxis

Severe anaphylactic reactions to neuromuscular blocking agents, including succinylcholine, have been reported. These reactions have, in some cases, been life-threatening and fatal. Due to the potential severity of these reactions, the necessary precautions, such as the immediate availability of appropriate emergency treatment, should be taken. Precautions should also be taken in those individuals who have had previous anaphylactic reactions to other neuromuscular blocking agents since cross-reactivity between neuromuscular blocking agents, both depolarizing and non-depolarizing, has been reported in this class of drugs.

Risk of Death due to Medication Errors

Administration of QUELICIN results in paralysis, which may lead to respiratory arrest and death; this progression may be more likely to occur in a patient for whom it is not intended. Confirm proper selection of intended product and avoid confusion with other injectable solutions that are present in critical care and other clinical settings. If another healthcare provider is administering the product, ensure that the intended dose is clearly labeled and communicated.

Hyperkalemia

(see BOX WARNING) Succinylcholine should be administered with GREAT CAUTION to patients suffering from electrolyte abnormalities and those who may have massive digitalis toxicity, because in these circumstances succinylcholine may induce serious cardiac arrhythmias or cardiac arrest due to hyperkalemia.

GREAT CAUTION should be observed if succinylcholine is administered to patients during the acute phase of injury following major burns, multiple trauma, extensive denervation of skeletal muscle, or upper motor neuron injury (see CONTRAINDICATIONS). The risk of hyperkalemia in these patients increases over time and usually peaks at 7 to 10 days after the injury. The risk is dependent on the extent and location of the injury. The precise time of onset and the duration of the risk period are undetermined. Patients with chronic abdominal infection, subarachnoid hemorrhage, or conditions causing degeneration of central and peripheral nervous systems should receive succinylcholine with GREAT CAUTION because of the potential for developing severe hyperkalemia.

Malignant Hyperthermia

Succinylcholine administration has been associated with acute onset of malignant hyperthermia, a potentially fatal hypermetabolic state of skeletal muscle. The risk of developing malignant hyperthermia following succinylcholine administration increases with the concomitant administration of volatile anesthetics. Malignant hyperthermia frequently presents as intractable spasm of the jaw muscles (masseter spasm) which may progress to generalized rigidity, increased oxygen demand, tachycardia, tachypnea and profound hyperpyrexia. Successful outcome depends on recognition of early signs, such as jaw muscle spasm, acidosis, or generalized rigidity to initial administration of succinylcholine for tracheal intubation, or failure of tachycardia to respond to deepening anesthesia. Skin mottling, rising temperature and coagulopathies may occur later in the course of the hypermetabolic process. Recognition of the syndrome is a signal for discontinuance of anesthesia, attention to increased oxygen consumption, correction of acidosis, support of circulation, assurance of adequate urinary output and institution of measures to control rising temperature. Intravenous dantrolene sodium is recommended as an adjunct to supportive measures in the management of this problem. Consult literature references and the dantrolene prescribing information for additional information about the management of malignant hyperthermic crisis. Continuous monitoring of temperature and expired CO2 is recommended as an aid to early recognition of malignant hyperthermia.

Other

In both adults and pediatric patients the incidence of bradycardia, which may progress to asystole, is higher following a second dose of succinylcholine. The incidence and severity of bradycardia is higher in pediatric patients than adults. Whereas bradycardia is common in pediatric patients after an initial dose of 1.5 mg/kg, bradycardia is seen in adults only after repeated exposure. Pretreatment with anticholinergic agents (e.g., atropine) may reduce the occurrence of bradyarrhythmias.

Succinylcholine causes an increase in intraocular pressure. It should not be used in instances in which an increase in intraocular pressure is undesirable (e.g., narrow angle glaucoma, penetrating eye injury) unless the potential benefit of its use outweighs the potential risk.

Succinylcholine is acidic (pH = 3.5) and should not be mixed with alkaline solutions having a pH greater than 8.5 (e.g., barbiturate solutions).

PRECAUTIONS (SEE BOXED WARNING)

General

When succinylcholine is given over a prolonged period of time, the characteristic depolarization block of the myoneural junction (Phase I block) may change to a block with characteristics superficially resembling a non-depolarizing block (Phase II block). Prolonged respiratory muscle paralysis or weakness may be observed in patients manifesting this transition to Phase II block. The transition from Phase I to Phase II block has been reported in 7 of 7 patients studied under halothane anesthesia after an accumulated dose of 2 to 4 mg/kg succinylcholine (administered in repeated, divided doses). The onset of Phase II block coincided with the onset of tachyphylaxis and prolongation of spontaneous recovery. In another study, using balanced anesthesia (N2O/O2/narcotic-thiopental) and succinylcholine infusion, the transition was less abrupt, with great individual variability in the dose of succinylcholine required to produce Phase II block. Of 32 patients studied, 24 developed Phase II block. Tachyphylaxis was not associated with the transition to Phase II block, and 50% of the patients who developed Phase II block experienced prolonged recovery.

When Phase II block is suspected in cases of prolonged neuromuscular blockade, positive diagnosis should be made by peripheral nerve stimulation, prior to administration of any anticholinesterase drug. Reversal of Phase II block is a medical decision which must be made upon the basis of the individual, clinical pharmacology and the experience and judgment of the physician. The presence of Phase II block is indicated by fade of responses to successive stimuli (preferably "train of four"). The use of an anticholinesterase drug to reverse Phase II block should be accompanied by appropriate doses of an anticholinergic drug to prevent disturbances of cardiac rhythm. After adequate reversal of Phase II block with an anticholinesterase agent, the patient should be continually observed for at least 1 hour for signs of return of muscle relaxation. Reversal should not be attempted unless: (1) a peripheral nerve stimulator is used to determine the presence of Phase II block (since anticholinesterase agents will potentiate succinylcholine-induced Phase I block), and (2) spontaneous recovery of muscle twitch has been observed for at least 20 minutes and has reached a plateau with further recovery proceeding slowly; this delay is to ensure complete hydrolysis of succinylcholine by plasma cholinesterase prior to administration of the anticholinesterase agent. Should the type of block be misdiagnosed, depolarization of the type initially induced by succinylcholine (i.e., Phase I block) will be prolonged by an anticholinesterase agent.

Succinylcholine should be employed with caution in patients with fractures or muscle spasm because the initial muscle fasciculations may cause additional trauma.

Succinylcholine may cause a transient increase in intracranial pressure; however, adequate anesthetic induction prior to administration of succinylcholine will minimize this effect.

Succinylcholine may increase intragastric pressure, which could result in regurgitation and possible aspiration of stomach contents.

Neuromuscular blockade may be prolonged in patients with hypokalemia or hypocalcemia.

Since allergic cross-reactivity has been reported in this class, request information from your patients about previous anaphylactic reactions to other neuromuscular blocking agents. In addition, inform your patients that severe anaphylactic reactions to neuromuscular blocking agents, including succinylcholine have been reported.

Reduced Plasma Cholinesterase Activity

Succinylcholine should be used carefully in patients with reduced plasma cholinesterase (pseudocholinesterase) activity. The likelihood of prolonged neuromuscular block following administration of succinylcholine must be considered in such patients (see DOSAGE & ADMINISTRATION).

Plasma cholinesterase activity may be diminished in the presence of genetic abnormalities of plasma cholinesterase (e.g., patients heterozygous or homozygous for atypical plasma cholinesterase gene), pregnancy, severe liver or kidney disease, malignant tumors, infections, burns, anemia, decompensated heart disease, peptic ulcer, or myxedema. Plasma cholinesterase activity may also be diminished by chronic administration of oral contraceptives, glucocorticoids, or certain monoamine oxidase inhibitors and by irreversible inhibitors of plasma cholinesterase (e.g., organophosphate insecticides, echothiophate, and certain antineoplastic drugs).

Patients homozygous for atypical plasma cholinesterase gene (1 in 2500 patients) are extremely sensitive to the neuromuscular blocking effect of succinylcholine. In these patients, a 5 to 10 mg test dose of succinylcholine may be administered to evaluate sensitivity to succinylcholine, or neuromuscular blockade may be produced by the cautious administration of a 1 mg/mL solution of succinylcholine by slow intravenous infusion. Apnea or prolonged muscle paralysis should be treated with controlled respiration.

Drug Interactions

Drugs which may enhance the neuromuscular blocking action of succinylcholine include: promazine, oxytocin, aprotinin, certain non-penicillin antibiotics, quinidine, β-adrenergic blockers, procainamide, lidocaine, trimethaphan, lithium carbonate, magnesium salts, quinine, chloroquine, diethylether, isoflurane, desflurane, metoclopramide and terbutaline. The neuromuscular blocking effect of succinylcholine may be enhanced by drugs that reduce plasma cholinesterase activity (e.g., chronically administered oral contraceptives, glucocorticoids, or certain monoamine oxidase inhibitors) or by drugs that irreversibly inhibit plasma cholinesterase (see PRECAUTIONS).

If other neuromuscular blocking agents are to be used during the same procedure, the possibility of a synergistic or antagonistic effect should be considered.

Carcinogenesis, Mutagenesis, Impairment of Fertility

There have been no long-term studies performed in animals to evaluate carcinogenic potential of succinylcholine. Genetic toxicology studies have not been completed to evaluate the genotoxic potential of succinylcholine. There are no studies to evaluate the potential impact of succinylcholine on fertility.

Pregnancy

Risk Summary

It is also not known whether succinylcholine can cause fetal harm when administered to a pregnant woman or can affect reproduction capacity. Animal reproduction studies have not been conducted with succinylcholine chloride. Succinylcholine should be given to a pregnant woman only if clearly needed.

The estimated background risk of major birth defects and miscarriage for the indicated population is unknown. All pregnancies have a background risk of birth defect, loss, or other adverse outcomes. In the U.S. general population, the estimated background risk of major birth defects and miscarriage in clinically recognized pregnancies is 2 to 4% and 15 to 20%, respectively.

Clinical Considerations

Plasma cholinesterase levels are decreased by approximately 24% during pregnancy and for several days postpartum. Therefore, a higher proportion of patients may be expected to show increased sensitivity (prolonged apnea) to succinylcholine when pregnant than when nonpregnant.

Labor and Delivery

Succinylcholine is commonly used to provide muscle relaxation during delivery by caesarean section. While small amounts of succinylcholine are known to cross the placental barrier, under normal conditions the quantity of drug that enters fetal circulation after a single dose of 1 mg/kg to the mother should not endanger the fetus. However, since the amount of drug that crosses the placental barrier is dependent on the concentration gradient between the maternal and fetal circulations, residual neuromuscular blockade (apnea and flaccidity) may occur in the newborn after repeated high doses to, or in the presence of atypical plasma cholinesterase in, the mother.

Nursing Mothers

It is not known whether succinylcholine is excreted in human milk. Because many drugs are excreted in human milk, caution should be exercised following succinylcholine administration to a nursing woman.

Pediatric Use

Safety and effectiveness of succinylcholine chloride have been established in pediatric patient age groups, neonate to adolescent. There are rare reports of ventricular dysrhythmias and cardiac arrest secondary to acute rhabdomyolysis with hyperkalemia in apparently healthy pediatric patients who receive succinylcholine (see BOX WARNING). Many of these pediatric patients were subsequently found to have a skeletal muscle myopathy such as Duchenne's muscular dystrophy whose clinical signs were not obvious. The syndrome often presents as sudden cardiac arrest within minutes after the administration of succinylcholine. These pediatric patients are usually, but not exclusively, males, and most frequently 8 years of age or younger. There have also been reports in adolescents. There may be no signs or symptoms to alert the practitioner to which patients are at risk. A careful history and physical may identify developmental delays suggestive of a myopathy. A preoperative creatine kinase could identify some but not all patients at risk. Due to the abrupt onset of this syndrome, routine resuscitative measures are likely to be unsuccessful. Careful monitoring of the electrocardiogram may alert the practitioner to peaked T-waves (an early sign). Administration of intravenous calcium, bicarbonate, and glucose with insulin, with hyperventilation have resulted in successful resuscitation in some of the reported cases. Extraordinary and prolonged resuscitative efforts have been effective in some cases. In addition, in the presence of signs of malignant hyperthermia, appropriate treatment should be initiated concurrently (see WARNINGS). Since it is difficult to identify which patients are at risk, it is recommended that the use of succinylcholine in pediatric patients should be reserved for emergency intubation or instances where immediate securing of the airway is necessary, e.g., laryngospasm, difficult airway, full stomach, or for intramuscular use when a suitable vein is inaccessible.

As in adults, the incidence of bradycardia in pediatric patients is higher following the second dose of succinylcholine. The incidence and severity of bradycardia is higher in pediatric patients than adults. Pre-treatment with anticholinergic agents, e.g., atropine, may reduce the occurrence of bradyarrhythmias.

Geriatric Use

Clinical studies of QUELICIN did not include sufficient numbers of subjects aged 65 and over to determine whether they respond differently from younger subjects. Other reported clinical experience has not identified differences in responses between the elderly and younger patients.

In general, dose selection for an elderly patient should be cautious, usually starting at the low end of the dosing range, reflecting the greater frequency of decreased hepatic, renal, or cardiac function, and of concomitant disease or other drug therapy.

ADVERSE REACTIONS

Adverse reactions to succinylcholine consist primarily of an extension of its pharmacological actions. Succinylcholine causes profound muscle relaxation resulting in respiratory depression to the point of apnea; this effect may be prolonged. Hypersensitivity reactions, including anaphylaxis, may occur in rare instances. The following additional adverse reactions have been reported: cardiac arrest, malignant hyperthermia, arrhythmias, bradycardia, tachycardia, hypertension, hypotension, hyperkalemia, prolonged respiratory depression or apnea, increased intraocular pressure, muscle fasciculation, jaw rigidity, postoperative muscle pain, rhabdomyolysis with possible myoglobinuric acute renal failure, excessive salivation, and rash.

There have been post-marketing reports of severe allergic reactions (anaphylactic and anaphylactoid reactions) associated with use of neuromuscular blocking agents, including succinylcholine. These reactions, in some cases, have been life threatening and fatal. Because these reactions were reported voluntarily from a population of uncertain size, it is not possible to reliably estimate their frequency (see WARNINGS and PRECAUTIONS).

OVERDOSAGE

Overdosage with succinylcholine may result in neuromuscular block beyond the time needed for surgery and anesthesia. This may be manifested by skeletal muscle weakness, decreased respiratory reserve, low tidal volume, or apnea. The primary treatment is maintenance of a patent airway and respiratory support until recovery of normal respiration is assured. Depending on the dose and duration of succinylcholine administration, the characteristic depolarizing neuromuscular block (Phase I) may change to a block with characteristics superficially resembling a non-depolarizing block (Phase II) (see PRECAUTIONS).

DOSAGE & ADMINISTRATION

The dosage of succinylcholine should be individualized and should always be determined by the clinician after careful assessment of the patient (see WARNINGS).

Parenteral drug products should be inspected visually for particulate matter and discoloration prior to administration whenever solution and container permit. Solutions which are not clear and colorless should not be used.

Risk of Medication Errors

Accidental administration of neuromuscular blocking agents may be fatal. Store QUELICIN with the cap and ferrule intact and in a manner that minimizes the possibility of selecting the wrong product.

Adults

For Short Surgical Procedures

The average dose required to produce neuromuscular blockade and to facilitate tracheal intubation is 0.6 mg/kg QUELICIN Injection given intravenously. The optimum dose will vary among individuals and may be from 0.3 to 1.1 mg/kg for adults. Following administration of doses in this range, neuromuscular blockade develops in about 1 minute; maximum blockade may persist for about 2 minutes, after which recovery takes place within 4 to 6 minutes. However, very large doses may result in more prolonged blockade. A 5 to 10 mg test dose may be used to determine the sensitivity of the patient and the individual recovery time (see PRECAUTIONS).

For Long Surgical Procedures

The dose of succinylcholine administered by infusion depends upon the duration of the surgical procedure and the need for muscle relaxation. The average rate for an adult ranges between 2.5 and 4.3 mg per minute.

Solutions containing from 1 to 2 mg per mL succinylcholine have commonly been used for continuous infusion. The more dilute solution (1 mg per mL) is probably preferable from the standpoint of ease of control of the rate of administration of the drug and, hence, of relaxation. This intravenous solution containing 1 mg per mL may be administered at a rate of 0.5 mg (0.5 mL) to 10 mg (10 mL) per minute to obtain the required amount of relaxation. The amount required per minute will depend upon the individual response as well as the degree of relaxation required. Avoid overburdening the circulation with a large volume of fluid. It is recommended that neuromuscular function be carefully monitored with a peripheral nerve stimulator when using succinylcholine by infusion in order to avoid overdose, detect development of Phase II block, follow its rate of recovery, and assess the effects of reversing agents (see PRECAUTIONS).

Intermittent intravenous injections of succinylcholine may also be used to provide muscle relaxation for long procedures. An intravenous injection of 0.3 to 1.1 mg/kg may be given initially, followed, at appropriate intervals, by further injections of 0.04 to 0.07 mg/kg to maintain the degree of relaxation required.

Pediatrics

For emergency tracheal intubation or in instances where immediate securing of the airway is necessary, the intravenous dose of succinylcholine is 2 mg/kg for infants and small pediatric patients; for older pediatric patients and adolescents the dose is 1 mg/kg (see BOXED WARNING and PRECAUTIONS: Pediatric Use). It is currently known that the effective dose of succinylcholine in pediatric patients may be higher than that predicted by body weight dosing alone. For example, the usual adult IV dose of 0.6 mg/kg is comparable to a dose of 2-3 mg/kg in neonates and infants to 6 months and 1-2 mg/kg in infants up to 2 years of age. This is thought to be due to the relatively large volume of distribution in the pediatric patient versus the adult patient.

Rarely, IV bolus administration of succinylcholine in infants and pediatric patients may result in malignant ventricular arrythmias and cardiac arrest secondary to acute rhabdomyolysis with hyperkalemia. In such situations, an underlying myopathy should be suspected.

Intravenous bolus administration of succinylcholine in infants or pediatric patients may result in profound bradycardia or, rarely, asystole. As in adults, the incidence of bradycardia in pediatric patients is higher following a second dose of succinylcholine. Whereas bradycardia is common in pediatric patients after an initial dose of 1.5 mg/kg, bradycardia is seen in adults only after repeated exposure. The occurrence of bradyarrhythmias may be reduced by pretreatment with atropine (see PRECAUTIONS: Pediatric Use).

Intramuscular Use

If necessary, succinylcholine may be given intramuscularly to infants, older pediatric patients or adults when a suitable vein is inaccessible. A dose of up to 3 to 4 mg/kg may be given, but not more than 150 mg total dose should be administered by this route. The onset of effect of succinylcholine given intramuscularly is usually observed in about 2 to 3 minutes.

Compatibility and Admixtures

Succinylcholine is acidic (pH 3.5) and should not be mixed with alkaline solutions having a pH greater than 8.5 (e.g., barbiturate solutions). Admixtures containing 1 to 2 mg/mL may be prepared by adding 1 g QUELICIN to 1,000 or 500 mL sterile solution, such as 5% Dextrose Injection, USP or 0.9% Sodium Chloride Injection, USP. Admixtures of QUELICIN must be used within 24 hours after preparation. Aseptic techniques should be used to prepare the diluted product. Admixtures of QUELICIN should be prepared for single patient use only. The unused portion of diluted QUELICIN should be discarded.

To prevent needle-stick injuries, needles should not be recapped, purposely bent, or broken by hand.

HOW SUPPLIED

SUCCINYLCHOLINE CHLORIDE INJECTION, USP is supplied in the following dosage forms.
NDC 51662-1353-1
SUCCINYLCHOLINE CHLORIDE INJECTION, USP 200mg (20mg/mL) 10mL VIAL

HF Acquisition Co LLC, DBA HealthFirst
Mukilteo, WA 98275

Also supplied in the following manufacture supplied dosage forms

QUELICIN™ (Succinylcholine Chloride Injection, USP) is supplied as a clear, colorless solution in the following concentrations and packages:

Refrigeration of the undiluted agent will assure full potency until expiration date. All units carry a date of expiration.

Store in refrigerator 2° to 8°C (36° to 46°F). The multi-dose vials are stable for up to 14 days at room temperature without significant loss of potency.

Distributed by Hospira, Inc., Lake Forest, IL 60045 USA

LAB-1246-2.0

Revised: 6/2018